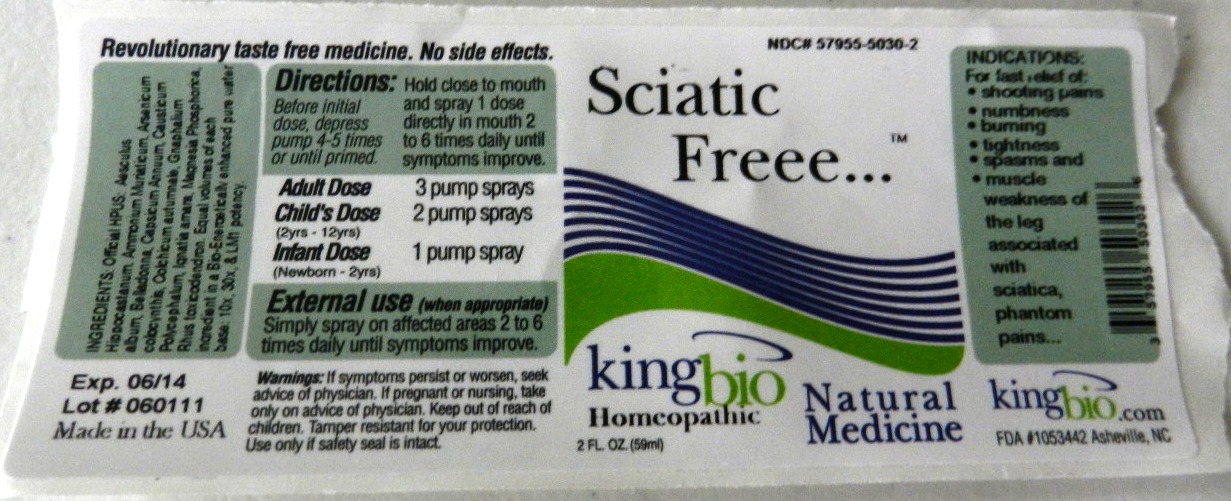 DRUG LABEL: Sciatici Freee
NDC: 57955-5030 | Form: LIQUID
Manufacturer: Kingbio
Category: homeopathic | Type: HUMAN OTC DRUG LABEL
Date: 20110614

ACTIVE INGREDIENTS: HORSE CHESTNUT 10 [hp_X]/1 mL; AMMONIUM CHLORIDE 10 [hp_X]/1 mL; ARSENIC TRIOXIDE 10 [hp_X]/1 mL; ATROPA BELLADONNA 10 [hp_X]/1 mL; CAPSICUM 10 [hp_X]/1 mL; CAUSTICUM 10 [hp_X]/1 mL; CITRULLUS COLOCYNTHIS FRUIT PULP 10 [hp_X]/1 mL; COLCHICUM AUTUMNALE BULB 10 [hp_X]/1 mL; PSEUDOGNAPHALIUM OBTUSIFOLIUM 10 [hp_X]/1 mL; STRYCHNOS IGNATII SEED 10 [hp_X]/1 mL; MAGNESIUM PHOSPHATE, DIBASIC TRIHYDRATE 10 [hp_X]/1 mL; TOXICODENDRON PUBESCENS LEAF 10 [hp_X]/1 mL
INACTIVE INGREDIENTS: WATER; CITRIC ACID MONOHYDRATE; POTASSIUM SORBATE

Sciatic Freee

OTC Active Ingredient

Aesculus Hippocastanum
Ammonium Muriaticum
Arsenicum album
Belladonna
Capsicum autumnale
Causticum
Colocynthis
Colchicum autumnale
Gnaphalium Polycephalum
Ignatia Amara
Magnesia Phosphorica
Rhus Toxicodendron
Reference image of sciatic freee.jpg

Inactive Ingredients

Citric Acid
Potassium Sorbate
Water

Reference image of sciatic freee.jpg

Dosage and administration

Directions:Hold close to mouth and spray 1 dose directly in mouth 2 to 6 times daily until symptoms improve.

- Adult Dose:3 pumps sprays
- Child's Dose:2 pumps sprays 2yrs to 12yrs
- Infant Dose:1pumps sprays newborn to 2yrs

Reference image of sciatic freee.jpg

Keep out of reach of children

Indication:If pregnant or nursing, take only on advice of physician. Keep out of reach of children. Tamper resistant for your protection. Use only if seal is intact.

Reference image of sciatic freee.jpg

warnings

Warnings:If symptoms persist or worsen, seek advice of physician. If pregnant or nursing, take only on advice of a physician. Keep out of reach of children. Tamper resistant for your protection. Use only if seal is intact.
Reference image of sciatic freee.jpg

OTC Purpose

Indications:

For fast relief of:

- shooting pain
- numbness
- tightness
- spasms
- muscle weakness of the leg associated with Associated with sciatica, phantom pains

Reference image of sciatic freee.jpg

Indications and usage

For fast releif of:

- shooting pains
- numbness
- burning
- tightness
- spasms and
- muscle weakness of the leg associated with sciatica, phantom pains...

Reference image of sciatic freee.jpg

Package Label Principal Display

Reference image of sciatic freee.jpg